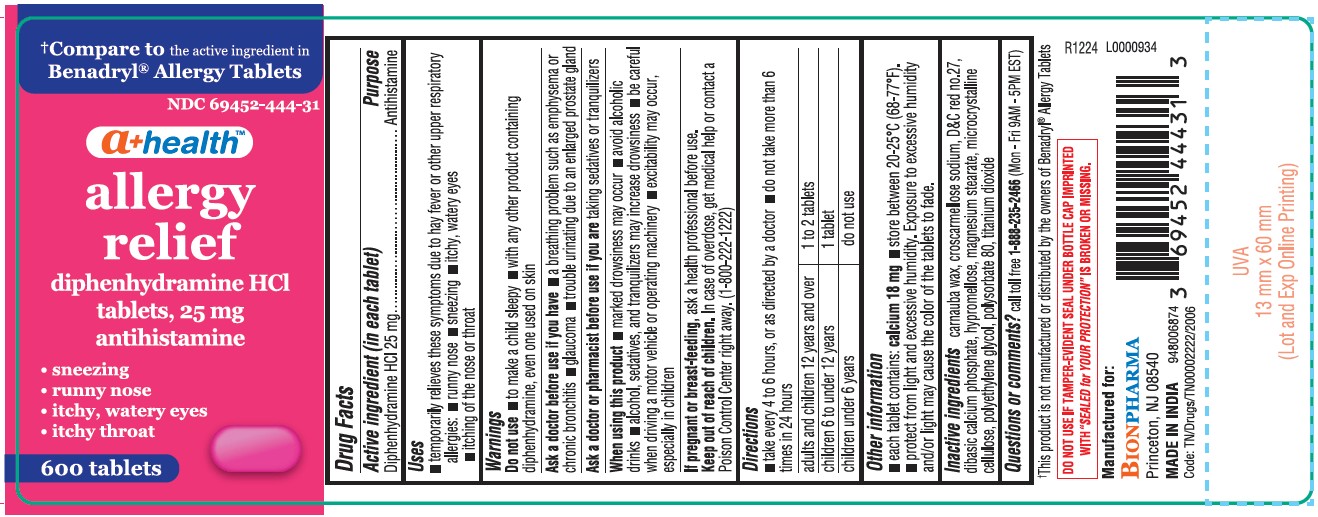 DRUG LABEL: Allergy Relief
NDC: 69452-444 | Form: TABLET
Manufacturer: BIONPHARMA INC.
Category: otc | Type: HUMAN OTC DRUG LABEL
Date: 20250623

ACTIVE INGREDIENTS: DIPHENHYDRAMINE HYDROCHLORIDE 25 mg/1 1
INACTIVE INGREDIENTS: POLYSORBATE 80; TITANIUM DIOXIDE; CARNAUBA WAX; CROSCARMELLOSE SODIUM; D&C RED NO. 27; ANHYDROUS DIBASIC CALCIUM PHOSPHATE; HYPROMELLOSE, UNSPECIFIED; MAGNESIUM STEARATE; MICROCRYSTALLINE CELLULOSE; POLYETHYLENE GLYCOL, UNSPECIFIED

Diphenhydramine HCl 25 mg tablet, A+ Health, allergy relief

Active ingredient (in each capsule)

Diphenhydramine HCl 25 mg

Purpose

Antihistamine

Uses

■ temporarily relieves these symptoms due to hay fever or the other upper respiratory allergies:
■ runny nose ■ sneezing ■ itchy, watery eyes ■ itching of the nose or throat

Warnings

Do not use ■ to make a child sleepy ■ with any other product containing
diphenhydramine, even one used on skin

Ask a doctor before use if you have

■ a breathing problem such as emphysema or chronic bronchitis ■ glaucoma
■ trouble urinating due to an enlarged prostate gland

Ask a doctor or pharmacist before use

if you are taking sedatives or tranquilizers.

When using this product

■ marked drowsiness may occur ■ avoid alcoholic drinks ■ alcohol, sedatives, and tranquilizers may increase drowsiness ■ be careful
when driving a motor vehicle or operating machinery ■ excitability may occur, especially in children

If pregnant or breast- feeding,

ask a health professional before use.

Keep out of reach of children.

In case of overdose, get medical help or contact a Poison Control Centre right away. (1-800-222-1222)

Directions

■ take every 4 to 6 hours, or as directed by a doctor ■ do not take more than 6 times in 24 hours

adults and children 12 years and over | 1 to 2 tablets
children 6 to under 12 years | 1 tablet
children under 6 years | do not use

Other information

■ each tablet contains: calcium 18 mg ■ store between 20-25°C (68-77°F).

Protect from light and excessive humidity. Exposure to excessive humidity and/or light may cause the color of the tablets to fade.

Inactive ingredients

carnauba wax, croscarmellose sodium, D&C red no.27, dibasic calcium phosphate, hypromellose, magnesium stearate, microcrystalline cellulose, polyethylene glycol, polysorbate 80, titanium dioxide

Questions or comments?

call toll-free 1-888-235-2466 (Mon - Fri 9AM - 5PM EST)

†This product is not manufactured or distributed by the owners of Benadryl® Allergy Tablets

DO NOT USE IF TAMPER-EVIDENT SEAL UNDER BOTTLE CAP IMPRINTED
WITH“SEALED for YOUR PROTECTION” IS BROKEN OR MISSING.

Manufactured for:
BIONPHARMA INC.
Princeton, NJ 08540

MADE IN INDIA

Code: TN/Drugs/TN00002222/2006

948006874

L0000934

R1224

600's count

†Compare to the active ingredient in
Benadryl® Allergy Tablets

NDC 69452-444-31

a+ healthTM
diphenhydramine HCl
tablets, 25 mg
antihistamine
allergy relief
• sneezing
• runny nose
• itchy, watery eyes
• itchy throat or nose

600 tablets